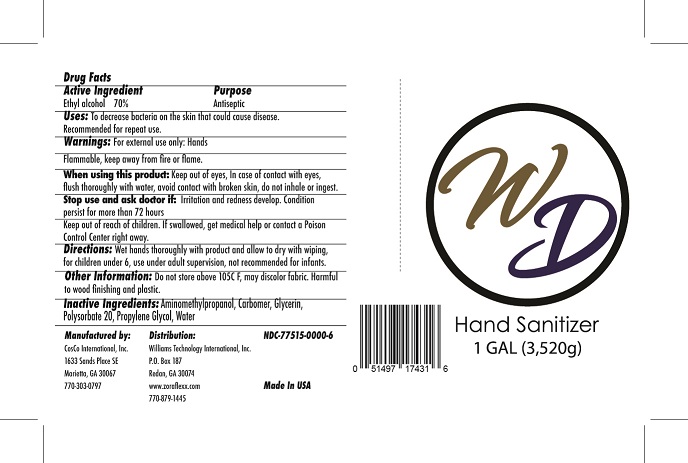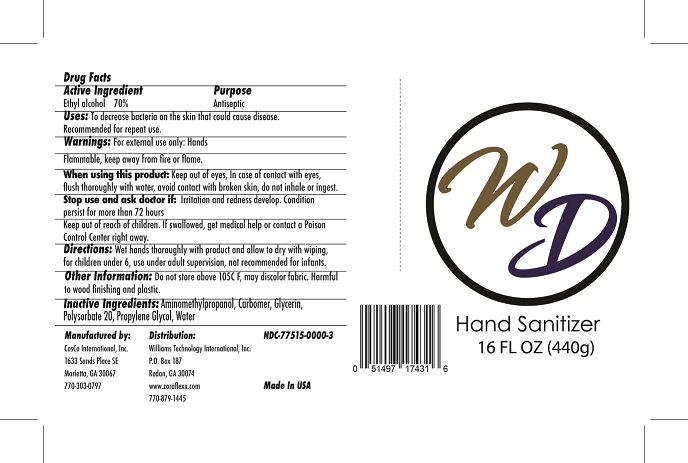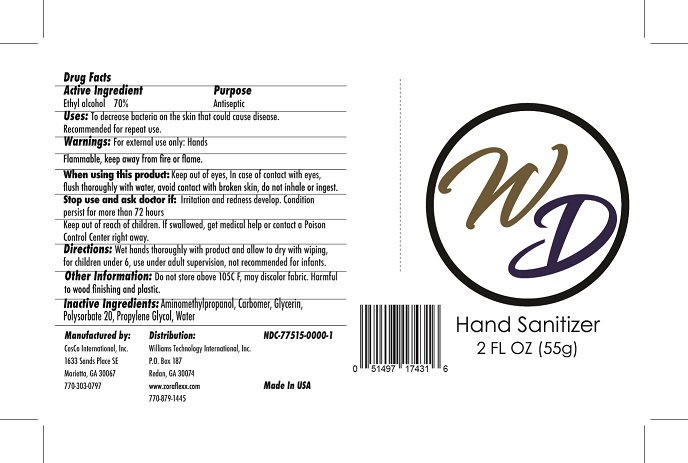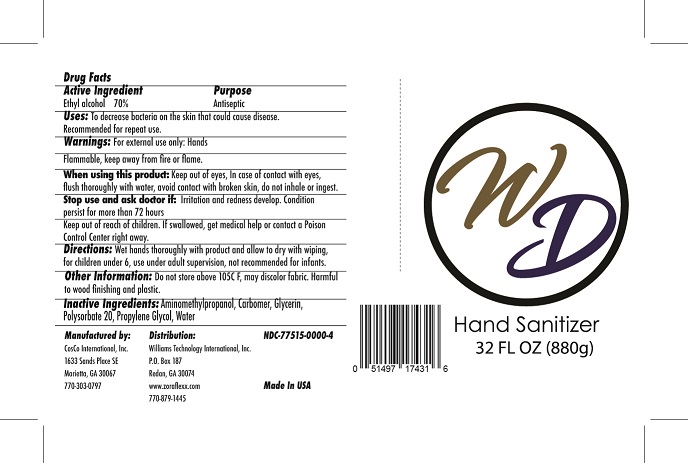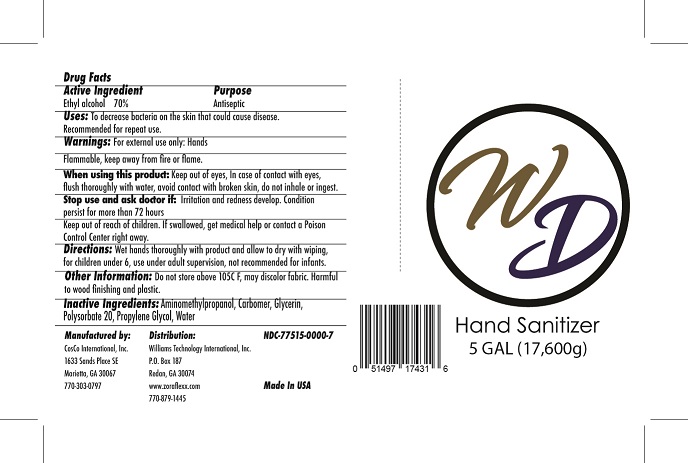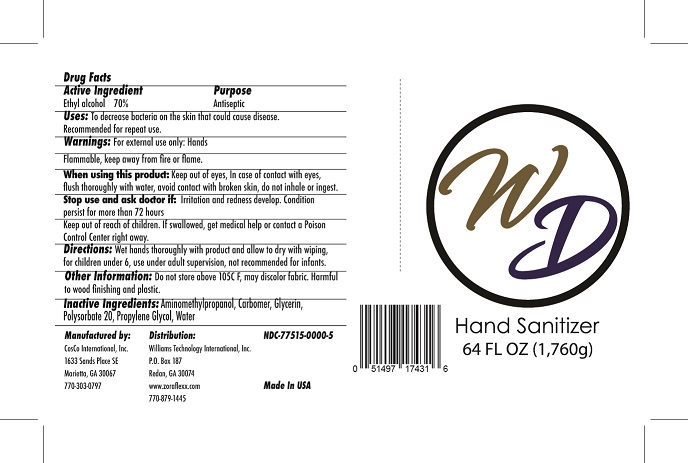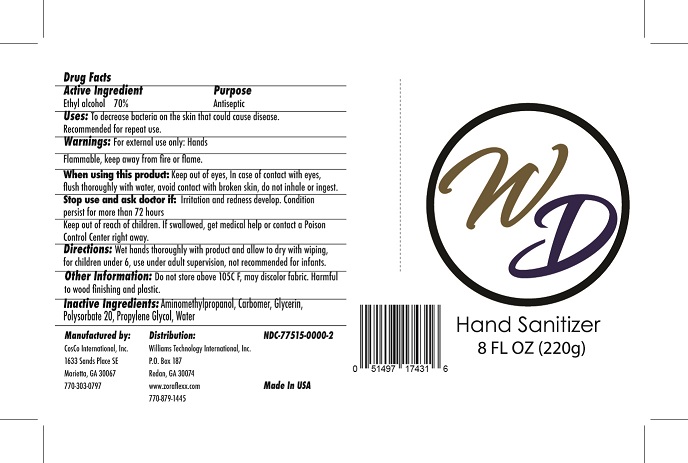 DRUG LABEL: WD Hand Sanitizer
NDC: 77515-0000 | Form: GEL
Manufacturer: Williams Technology International, Inc
Category: otc | Type: HUMAN OTC DRUG LABEL
Date: 20200601

ACTIVE INGREDIENTS: ALCOHOL 75 L/100 L
INACTIVE INGREDIENTS: AMINOMETHYLPROPANOL; CARBOMER HOMOPOLYMER, UNSPECIFIED TYPE; GLYCERIN; PHENOXYETHANOL; ETHYLHEXYLGLYCERIN

Active Ingredient(s)

Alcohol 75% v/v. Purpose: Antiseptic

Purpose

Antiseptic

Uses:

To decrease bacteria on the skin that could cause disease. Recommended for repeat use.

Warnings:

For external use only: Hands

Flammable, Keep away from fire or flame

When using this product keep out of eyes, In case of contact with eyes, rinse eyes thoroughly with water, avoid contact with broken skin, do not inhale or ingest.

Stop use and ask a doctor if irritation or redness develop. Condition persist for more than 72 hours.

Keep out of reach of children. If swallowed, get medical help or contact a Poison Control Center right away.

Directions

Wet hands thoroughly with product and allow to dry with wiping,

for children under 6, use under adult supervision, not recommended for infants.

Other information:

Do not store above 105°F, may discolor fabric. Harmful to wood finishing and plastic.

Inactive ingredients:

Aminomethylpropanol, Carbomer, Glycerin, Polysorbate 20, Propylene Glycol, Water